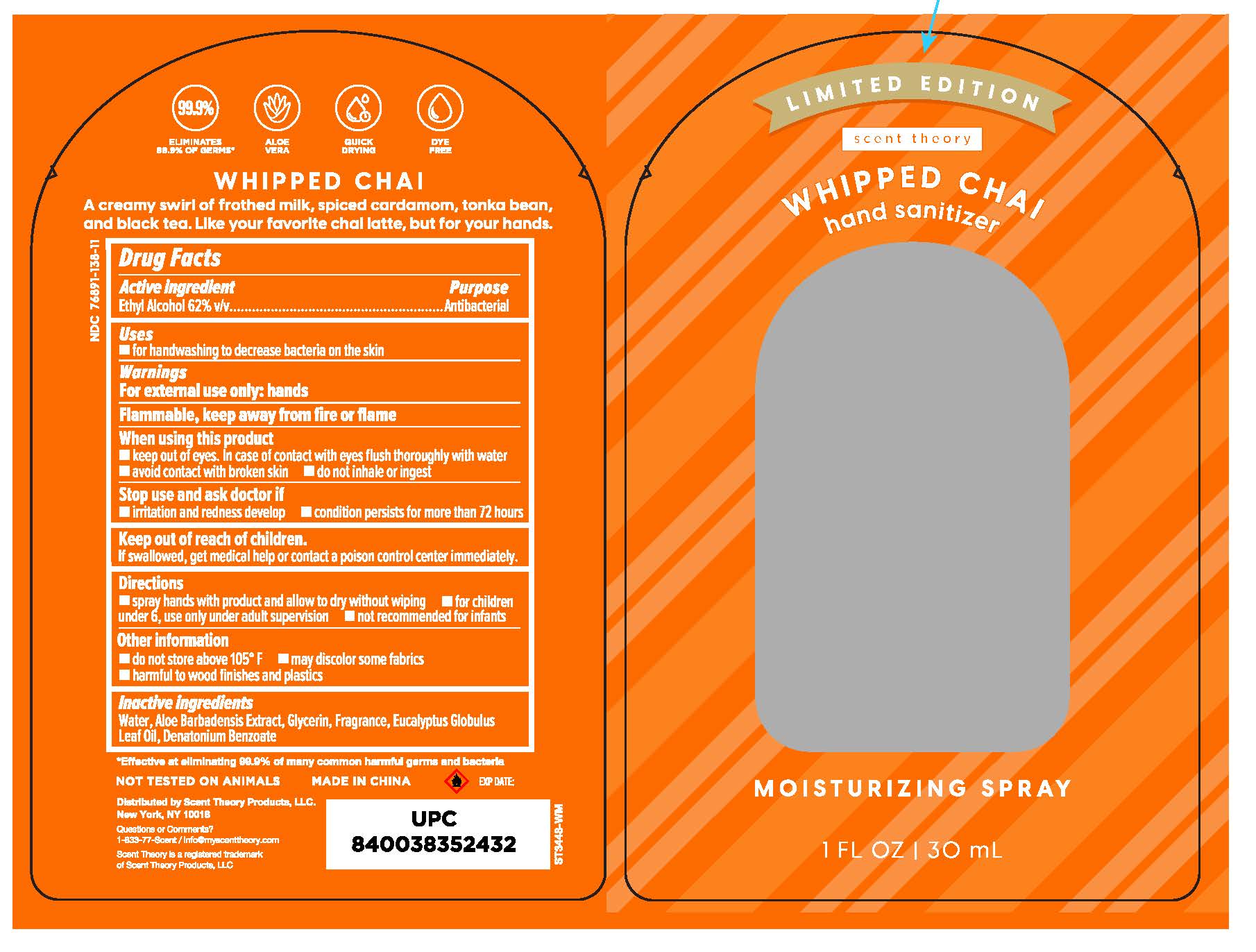 DRUG LABEL: Hand Sanitizer
NDC: 76891-144 | Form: SPRAY
Manufacturer: Scent Theory Products LLC
Category: otc | Type: HUMAN OTC DRUG LABEL
Date: 20250520

ACTIVE INGREDIENTS: ALCOHOL 62 mL/100 mL
INACTIVE INGREDIENTS: WATER; ALOE VERA LEAF; GLYCERIN; DENATONIUM BENZOATE; EUCALYPTUS GLOBULUS LEAF

Hand Sanitizer Whipped Chai

Active ingredients

ETHYL ALCOHOL 62% V/V

Purpose

ANTISEPTIC

Uses

FOR HANDWASHING TO DECREASE BACTERIA ON THE SKIN.

Warnings

FOR EXTERNAL USE ONLY: HANDS
FLAMMABLE, KEEP AWAY FROM FIRE OR FLAME.

WHEN USING THIS PRODUCT

- KEEP OUT OF EYES. IN CASE OF CONTACT WITH EYES, FLUSH THOROUGHLY WITH WATER.
- AVOID CONTACT WITH BROKEN SKIN.
- DO NOT INHALE OR INGEST.

STOP USE AND ASK A DOCTOR IF

- IRRITATION AND REDNESS DEVELOP
- CONDITION PERSISTS FOR MORE THAN 72 HOURS

Directions

SPRAY HANDS WITH PRODUCT AND ALLOW TO DRY WITHOUT WIPING
FOR CHILDREN UNDER 6, USE ONLY UNDER ADULT SUPERVISION
NOT RECOMMENDED FOR INFANTS

Other information

DO NOT STORE ABOVE 105°F
MAY DISCOLOR SOME FABRICS
HARMFUL TO WOOD FINISHES AND PLASTICS

Inactive ingredients

WATER, ALOE BARBADENSIS LEAF JUICE, GLYCERIN, FRAGRANCE, EUCALYPTUS GLOBULUS LEAF OIL, DENATONIUM BENZOATE